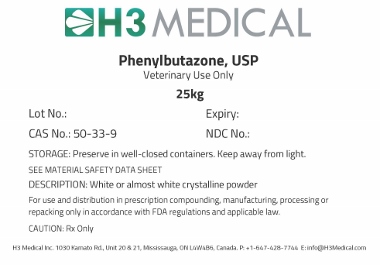 DRUG LABEL: Phenylbutazone
NDC: 63732-2039 | Form: POWDER
Manufacturer: H3 Medical Inc
Category: other | Type: BULK INGREDIENT - ANIMAL DRUG
Date: 20171121

ACTIVE INGREDIENTS: PHENYLBUTAZONE 1 g/1 g

Phenylbutazone